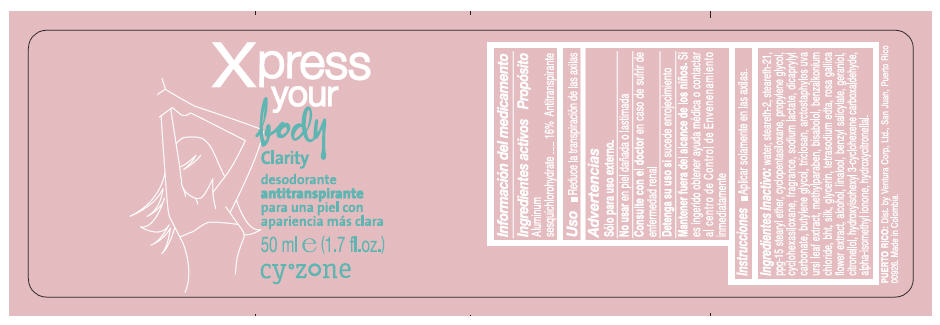 DRUG LABEL: CYZONE XPRESS YOUR BODY CLARITY
NDC: 13537-989 | Form: EMULSION
Manufacturer: Ventura Corporation LTD
Category: otc | Type: HUMAN OTC DRUG LABEL
Date: 20160809

ACTIVE INGREDIENTS: ALUMINUM SESQUICHLOROHYDRATE 0.16 g/1 mL
INACTIVE INGREDIENTS: WATER; STEARETH-2; STEARETH-21; PPG-15 STEARYL ETHER; CYCLOMETHICONE 5; PROPYLENE GLYCOL; CYCLOMETHICONE 6; SODIUM LACTATE; DICAPRYLYL CARBONATE; BUTYLENE GLYCOL; TRICLOSAN; ARCTOSTAPHYLOS UVA-URSI LEAF; METHYLPARABEN; LEVOMENOL; BENZALKONIUM CHLORIDE; BUTYLATED HYDROXYTOLUENE; BOMBYX MORI FIBER; GLYCERIN; EDETATE SODIUM; ROSA GALLICA FLOWER; ALCOHOL; LINALOOL, (+/-)-; BENZYL SALICYLATE; GERANIOL; .BETA.-CITRONELLOL, (R)-; HYDROXYISOHEXYL 3-CYCLOHEXENE CARBOXALDEHYDE; ISOMETHYL-.ALPHA.-IONONE; HYDROXYCITRONELLAL

CYZONE XPRESS YOUR BODY CLARITY

Información del medicamento

Ingredientes activos

Aluminum Sesquichlorohydrate 16%

Propósito

Antitranspirante

Uso

- Reduce la transpiración de las axilas

Advertencias

- Sólo para uso externo.

DO NOT USE

- No usar en piel dañada o lastimada

ASK DOCTOR

- Consulte con el doctor en caso de sufrir de enfermedad renal

STOP USE

- Detenga su uso si sucede enrojecimiento

KEEP OUT OF REACH OF CHILDREN

- Mantener fuera del alcance de los niños. Si es ingerido obtener ayuda médica o contactar al centro de Control de Envenenamiento inmediatamente

Instrucciones

- Aplicar solamente en las axilas.

Ingredientes inactivo

WATER, STEARETH-2, STEARETH-21, PPG-15 STEARYL ETHER, CYCLOPENTASILOXANE, PROPYLENE GLYCOL, CYCLOHEXASILOXANE, FRAGRANCE, SODIUM LACTATE, DICAPRYLYL CARBONATE, BUTYLENE GLYCOL, TRICLOSAN, ARCTOSTAPHYLOS UVA URSI LEAF EXTRACT, METHYLPARABEN, BISABOLOL, BENZALKONIUM CHLORIDE, BHT, SILK, GLYCERIN, TETRASODIUM EDTA, ROSA GALLICA FLOWER EXTRACT, ALCOHOL, LINALOOL, BENZYL SALICYLATE, GERANIOL, CITRONELLOL, HYDROXYISOHEXYL 3-CYCLOHEXENE CARBOXALDEHYDE, ALPHA-ISOMETHYL IONONE, HYDROXYCITRONELLAL.

Dist. by Ventura Corp, Ltd., San Juan, Puerto Rico
00926.

PRINCIPAL DISPLAY PANEL - 50 ml Bottle Label

Xpress
your
body

Clarity

desodorante
antitranspirante
para una piel con
apariencia más clara

50 ml e (1.7 fl.oz.)

cy°zone